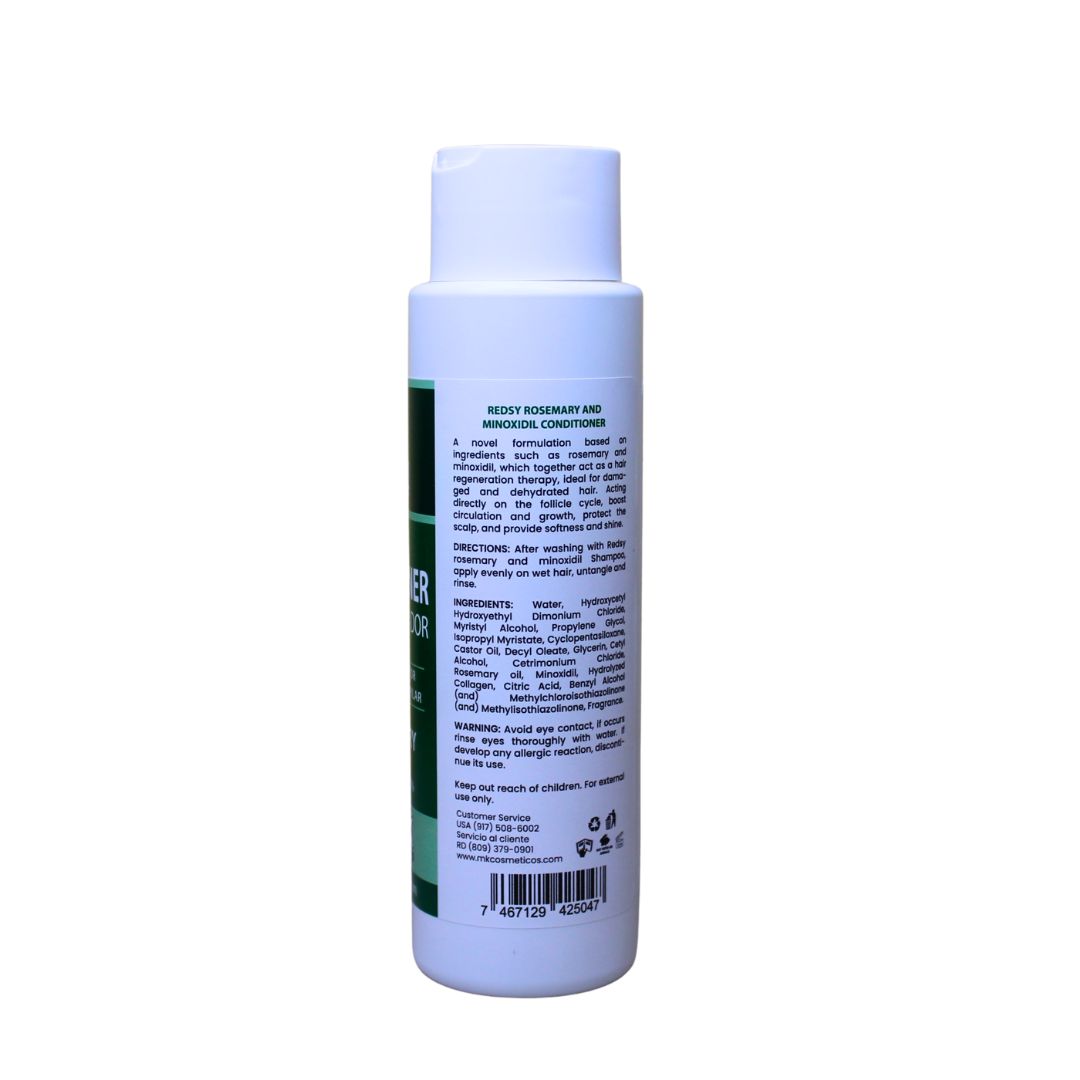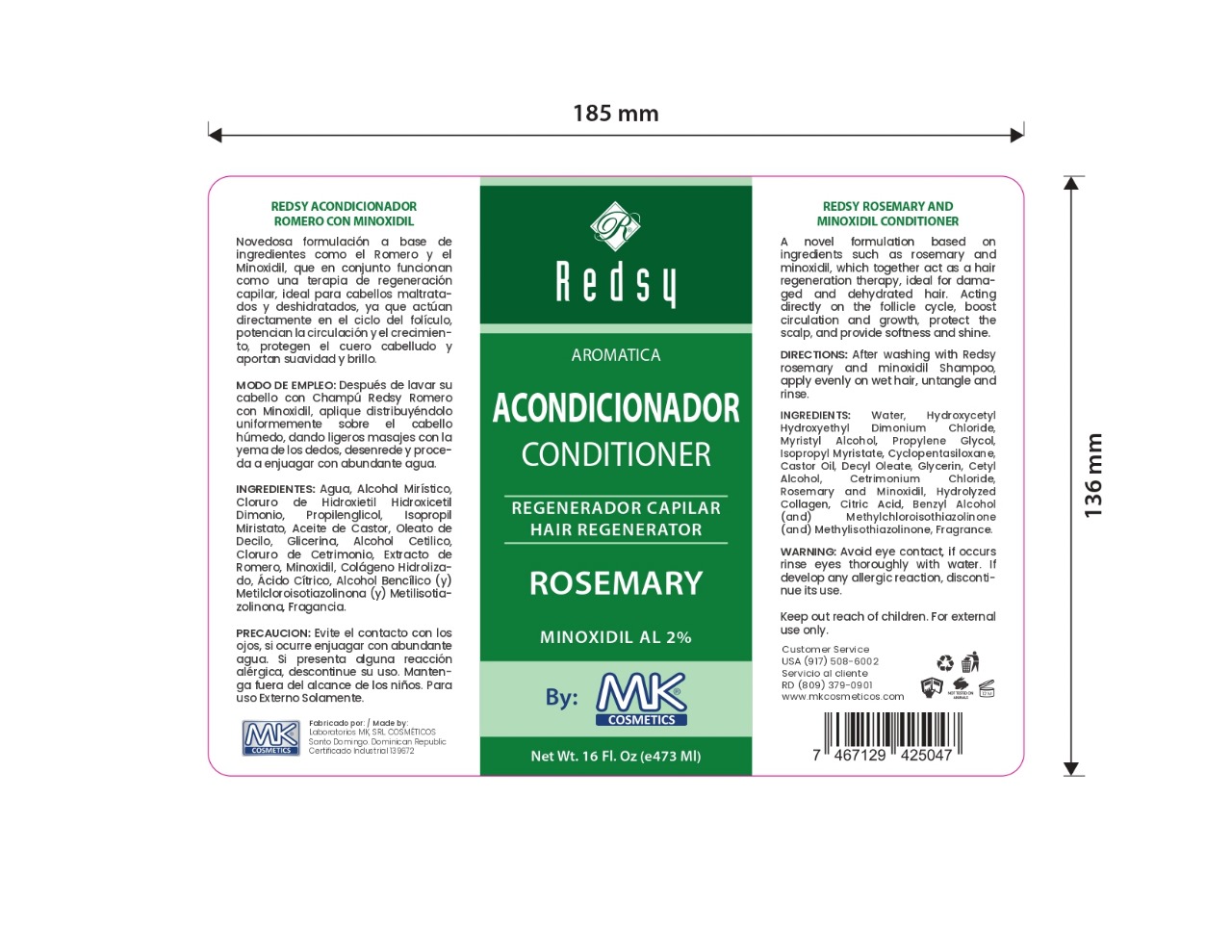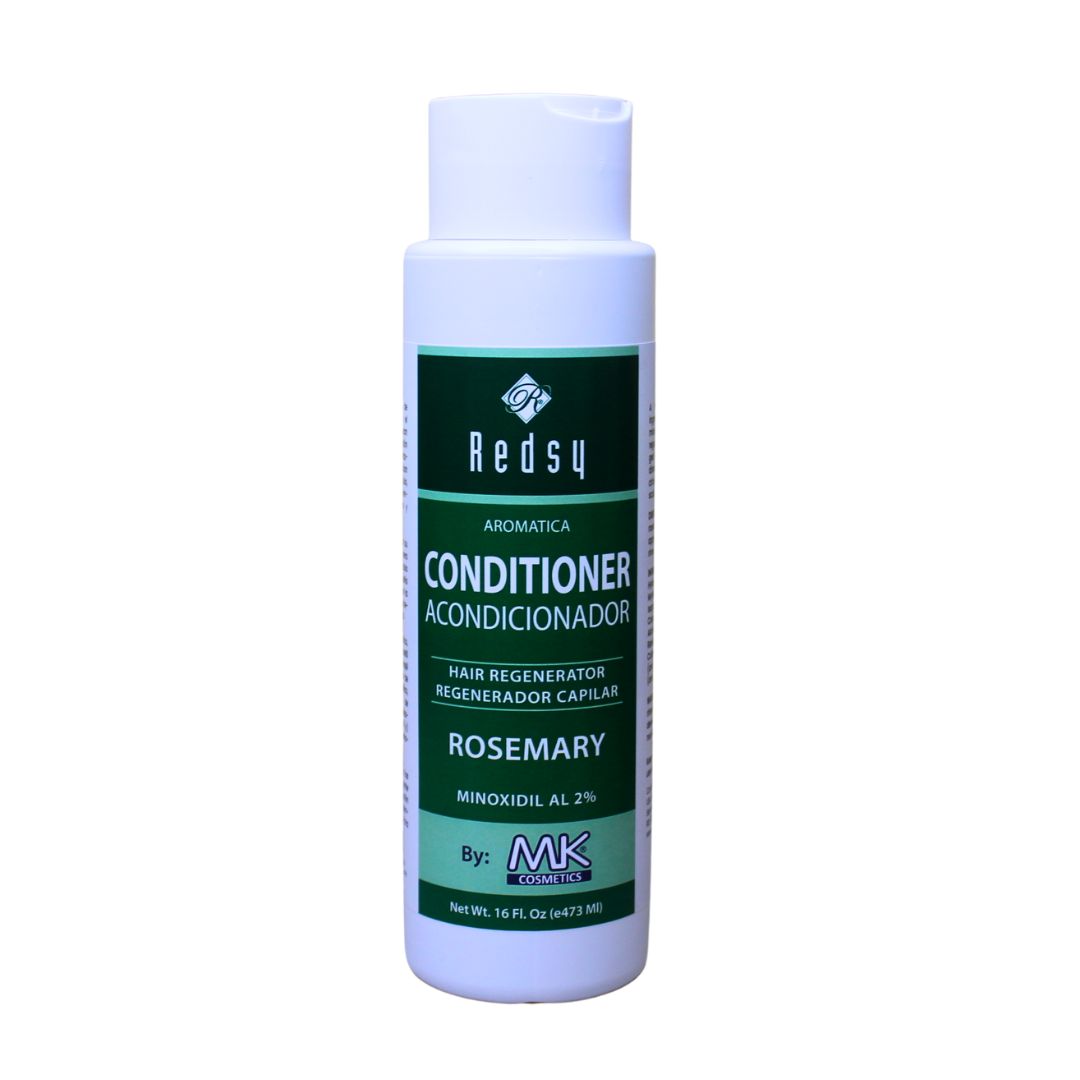 DRUG LABEL: aromatica hair acondicionador romero con minoxidil
NDC: 87022-012 | Form: RINSE
Manufacturer: LABORATORIO MK SRL
Category: otc | Type: HUMAN OTC DRUG LABEL
Date: 20251001

ACTIVE INGREDIENTS: MINOXIDIL 2 mg/473 mL
INACTIVE INGREDIENTS: BENZYL ALCOHOL; WATER; MYRISTYL ALCOHOL; PROPYLENE GLYCOL 1,2-DISTEARATE; ISOPROPYL MYRISTATE; HYDROLYZED PORCINE COLLAGEN (ENZYMATIC; 3000 MW); GLYCERIN; HYDROXYCETYL HYDROXYETHYL DIMONIUM CHLORIDE; CYCLOPENTASILOXANE; DECYL OLEATE; CETYL ALCOHOL; ROSEMARY OIL; CITRIC ACID; METHYLCHLOROISOTHIAZOLINONE; METHYLISOTHIAZOLINONE; CETRIMONIUM CHLORIDE; CASTOR OIL

INDICATIONS AND USAGE

After washing with Redsy rosemary and minoxidil Shampoo, apply evenly on wet hair, untangle and rinse.

INACTIVE INGREDIENT

Water, Hydroxycetyl Hydroxyethyl Dimonium Chloride, Myristyl Alcohol, Propylene Glycol, Isopropyl Myristate, Cyclopentasiloxane, Castor Oil, Decyl Oleate, Glycerin, Cetyl Alcohol, Cetrimonium Chloride, Rosemary, Hydrolyzed Collagen, Citric Acid, Benzyl Alcohol (and) Methylchloroisothiazolinone (and) Methylisothiazolinone, Fragrance.

WARNINGS

Avoid eye contact, if occurs rinse eyes thoroughly with water. If develop any allergic reaction, discontinue its use.

INFORMATION FOR OWNERS/CAREGIVERS

Customer Service USA (917)508-6002

Customer Service RD (809)379-0900

www.mkcosmeticos.com

DOSAGE AND ADMINISTRATION

After washing with Redsy rosemary and minoxidil Shampoo, apply evenly on wet hair, untangle and rinse.

KEEP OUT OF REACH OF CHILDREN

Keep out reach of children. For external use only.

PURPOSE

Aromatica hair regenerator

PACKAGE LABEL

aromatica conditioner hair regenerator rosemary with minoxidil